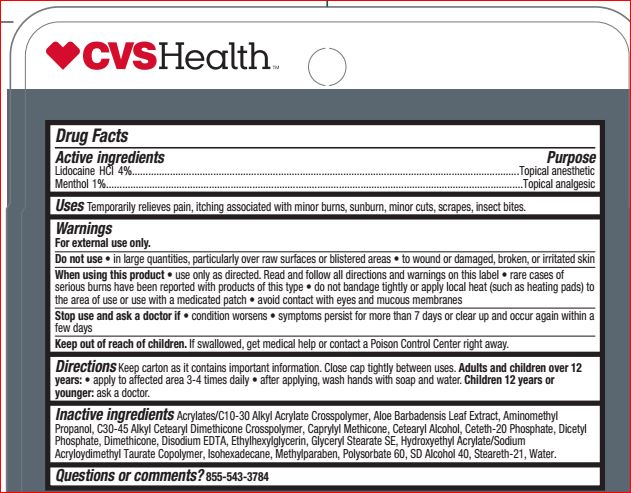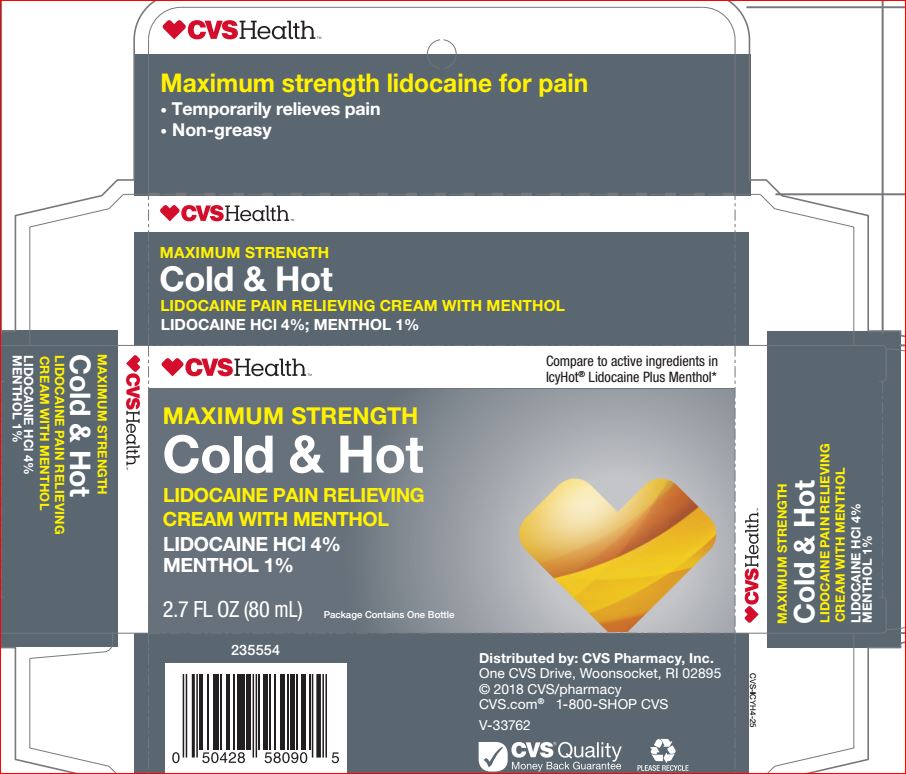 DRUG LABEL: Maximum Strength Cold and Hot
NDC: 69842-667 | Form: CREAM
Manufacturer: CVS
Category: otc | Type: HUMAN OTC DRUG LABEL
Date: 20180426

ACTIVE INGREDIENTS: LIDOCAINE HYDROCHLORIDE 4 g/100 mL; Menthol 1 g/100 mL
INACTIVE INGREDIENTS: ALOE VERA LEAF; AMINOMETHYLPROPANOL; CAPRYLYL TRISILOXANE; CETOSTEARYL ALCOHOL; Ceteth-20 Phosphate; DIHEXADECYL PHOSPHATE; Dimethicone; EDETATE DISODIUM; Ethylhexylglycerin; GLYCERYL STEARATE SE; Isohexadecane; Methylparaben; Polysorbate 60; ALCOHOL; Steareth-21; Water

Drug Facts

Active ingredients Purpose

Lidocaine HCL 4%............................Topical analgesic

Menthol 1%.....................................Topical analgesic

Uses

Temporarily relieves pain and itching due to:
• sunburn • minor burns • minor cuts • scrapes • insect bites

Warnings For external use only

Do not use • in large quantities, particularly over raw surface or blistered areas

When using this product

•avoid contact with eyes

• do not apply to wounds or damages skin
• do not bandage tightly or use with a heating pad
• use only as directed

Stop use and ask a doctor if
• condition worsens
• symptoms last more than 7 days or clear up and occur again within a few days

Keep out of reach of the children
If product is swallowed, get medical help or contact a Poison Control Center right away

Directions

• adults and children 12 years of age and older: spray on affected area, not more than 3 to 4 times daily
• children under 12 years of age: consult a doctor

Inactive ingredients

Acrylates/C10-30 Alkyl Acrylate Crosspolymer
Aloe Barbadensis Leaf Extract
Aminomethyl Propanol
C30-45 Alkyl Cetearyl Dimethicone Crosspolymer
Caprylyl Methicone
Cetearyl Alcohol
Ceteth-20 Phosphate
Dicetyl Phosphate
Dimethicone
Disodium EDTA
Ethylhexylglycerin
Glyceryl Stearate SE
Hydroxyethyl Acrylate/Sodium Acryloydimethyl Taurate Copolymer
Isohexadecane
Methylparaben
Polysorbate 60
SD Alcohol 40
Steareth-21
Water